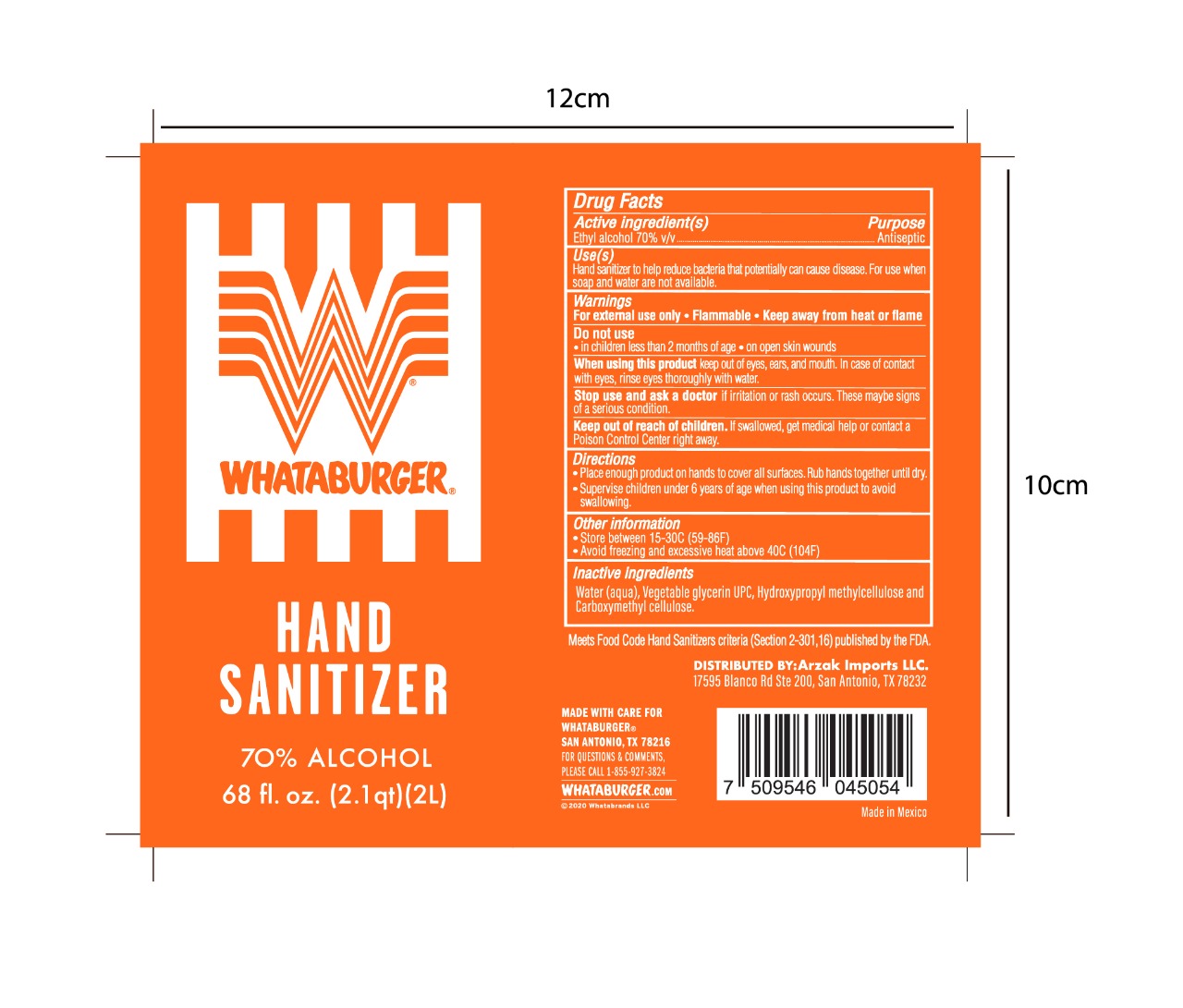 DRUG LABEL: HAND SANITIZER
NDC: 80535-0002 | Form: GEL
Manufacturer: FARMACIA SAN ARCANGEL, S.A DE C.V
Category: otc | Type: HUMAN OTC DRUG LABEL
Date: 20200923

ACTIVE INGREDIENTS: ALCOHOL 70 mL/100 mL
INACTIVE INGREDIENTS: WATER; HYPROMELLOSE 2208 (60000 MPA.S); GLYCERIN; CARBOXYMETHYLCELLULOSE

Active Ingredients

Ethyl alcohol 70% v/v

Purpose

Antiseptic

Uses

Hand sanitizer to help reduce bacteria that potentially can cause disease. For use when soap and water are not available

Warnings

For external use only . flammable - keep away from heat or flame

Do not use

In children less than 2 months of age - on open skin wounds

When using this product

keep out of eyes, ears, and mouth. In case of contact with eyes, rinse eyes throrugly with water

Stop use and ask a doctor

if irritation or rash occurs. These maybe signs of a serious condition.

keep out of reach of children

if swallowed, get medical help or contact a poison control center right away.

Directions

Put enough product on hands to cover all surfaces. Rub hands together until dry.

Supervise children under 6 years of age when using this product to avoid swallowing

Other information

Store between 15-30C (58-86F)

Avoid freezing and excesive heat above 40C (104F)

Inactive ingredients

Water (aqua), Vegetable Glycerine UPC, Hudroxypropyl methylcellulose and carboxymethylcellulose.

Principal Display

Hand sanitizer

70% alcohol

68 fl. oz. (2.1qt) (2L)